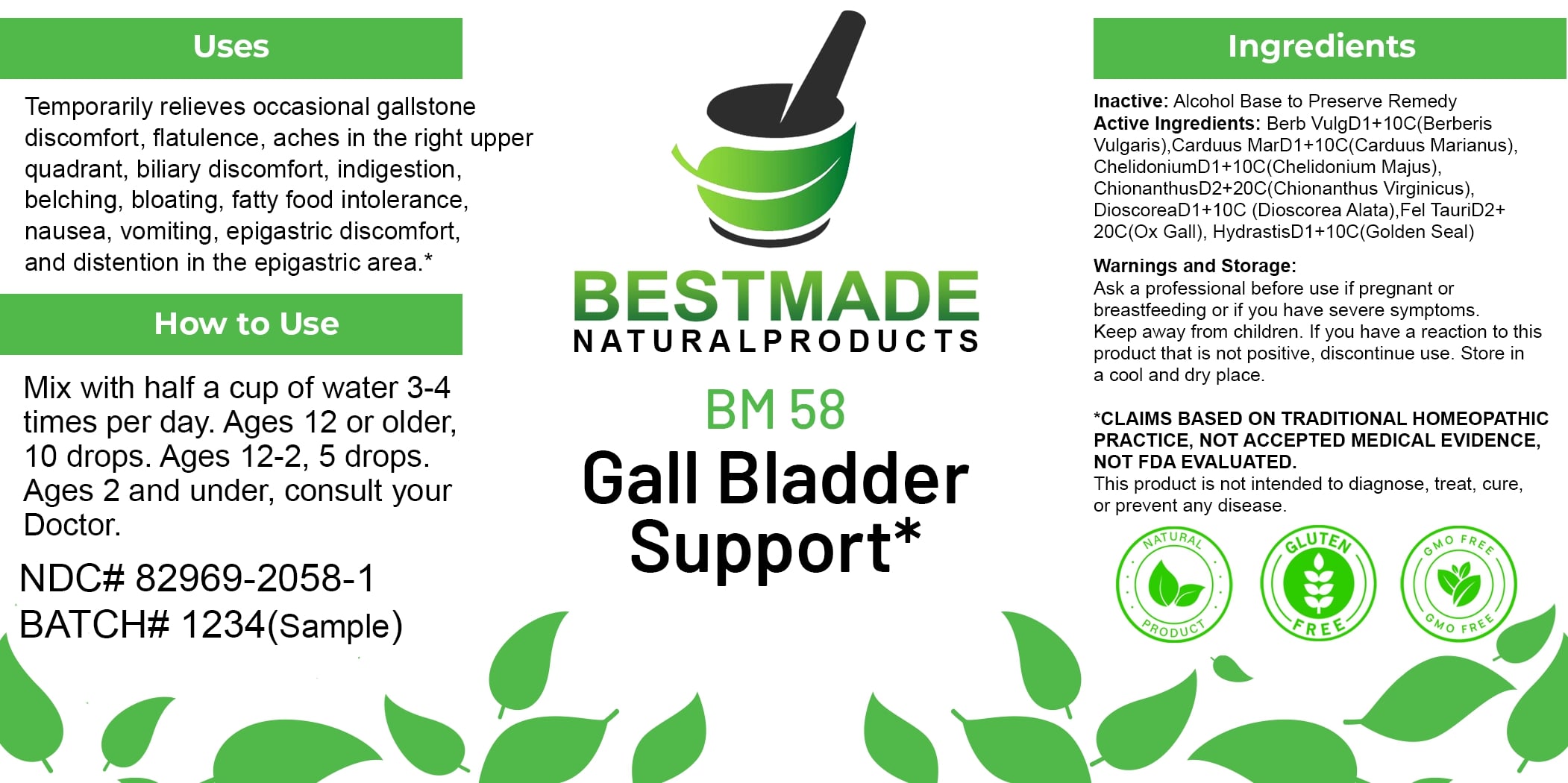 DRUG LABEL: Bestmade Natural Products BM58
NDC: 82969-2058 | Form: LIQUID
Manufacturer: Bestmade Natural Products
Category: homeopathic | Type: HUMAN OTC DRUG LABEL
Date: 20250124

ACTIVE INGREDIENTS: DIOSCOREA ALATA WHOLE 10 [hp_C]/20 [hp_C]; GOLDENSEAL 10 [hp_C]/20 [hp_C]; BERBERIS VULGARIS ROOT BARK 10 [hp_C]/20 [hp_C]; CHIONANTHUS VIRGINICUS WHOLE 20 [hp_C]/20 [hp_C]; CHELIDONIUM MAJUS 10 [hp_C]/20 [hp_C]; MILK THISTLE 10 [hp_C]/20 [hp_C]; BOS TAURUS BILE 20 [hp_C]/20 [hp_C]
INACTIVE INGREDIENTS: ALCOHOL 20 [hp_C]/20 [hp_C]

BM58

DOSAGE AND ADMINISTRATION

How to Use

Mix with half a cup of water 3-4 times per day. Ages 12 or older, 10 drops. Ages 12-2, 5 drops. Ages 2 and under, consult your Doctor.

INACTIVE INGREDIENT

Ingredients

Inactive: Alcohol Base to Preserve Remedy

ACTIVE INGREDIENT

Active Ingredients: Berb Vulg D1+10C (Berberis Vulgaris), Carduus Mar D1+10C (Carduus Marianus), Chelidonium D1+10C (Chelidonium Majus), Chionanthus D2+20C (Chionanthus Virginicus), Dioscorea D1+10C (Dioscorea Alata), Fel Tauri D2+20C (Ox Gall), Hydrastis D1+10C (Golden Seal)

Uses

Temporarily relieves occasional gallstone discomfort, flatulence, aches in the right upper quadrant, biliary discomfort, indigestion, belching, bloating, fatty food intolerance, nausea, vomiting, epigastric discomfort, and distention in the epigastric area.*

*CLAIMS BASED ON TRADITIONAL HOMEOPATHIC PRACTICE, NOT ACCEPTED MEDICAL EVIDENCE. NOT FDA EVALUATED.

This product is not intended to diagnose, treat, cure, or prevent any disease.

Uses

Temporarily relieves occasional gallstone discomfort, flatulence, aches in the right upper quadrant, biliary discomfort, indigestion, belching, bloating, fatty food intolerance, nausea, vomiting, epigastric discomfort, and distention in the epigastric area.*

*CLAIMS BASED ON TRADITIONAL HOMEOPATHIC PRACTICE, NOT ACCEPTED MEDICAL EVIDENCE. NOT FDA EVALUATED.

This product is not intended to diagnose, treat, cure, or prevent any disease.

KEEP OUT OF REACH OF CHILDREN

Warnings and Storage:

Ask a professional before use if pregnant or breastfeeding or if you have severe symptoms. Keep away from children. If you have a reaction to this product that is not positive, discontinue use. Store in a cool and dry place.

Warnings and Storage:

Ask a professional before use if pregnant or breastfeeding or if you have severe symptoms. Keep away from children. If you have a reaction to this product that is not positive, discontinue use. Store in a cool and dry place.

*CLAIMS BASED ON TRADITIONAL HOMEOPATHIC PRACTICE, NOT ACCEPTED MEDICAL EVIDENCE. NOT FDA EVALUATED.

This product is not intended to diagnose, treat, cure, or prevent any disease.

Entire package label